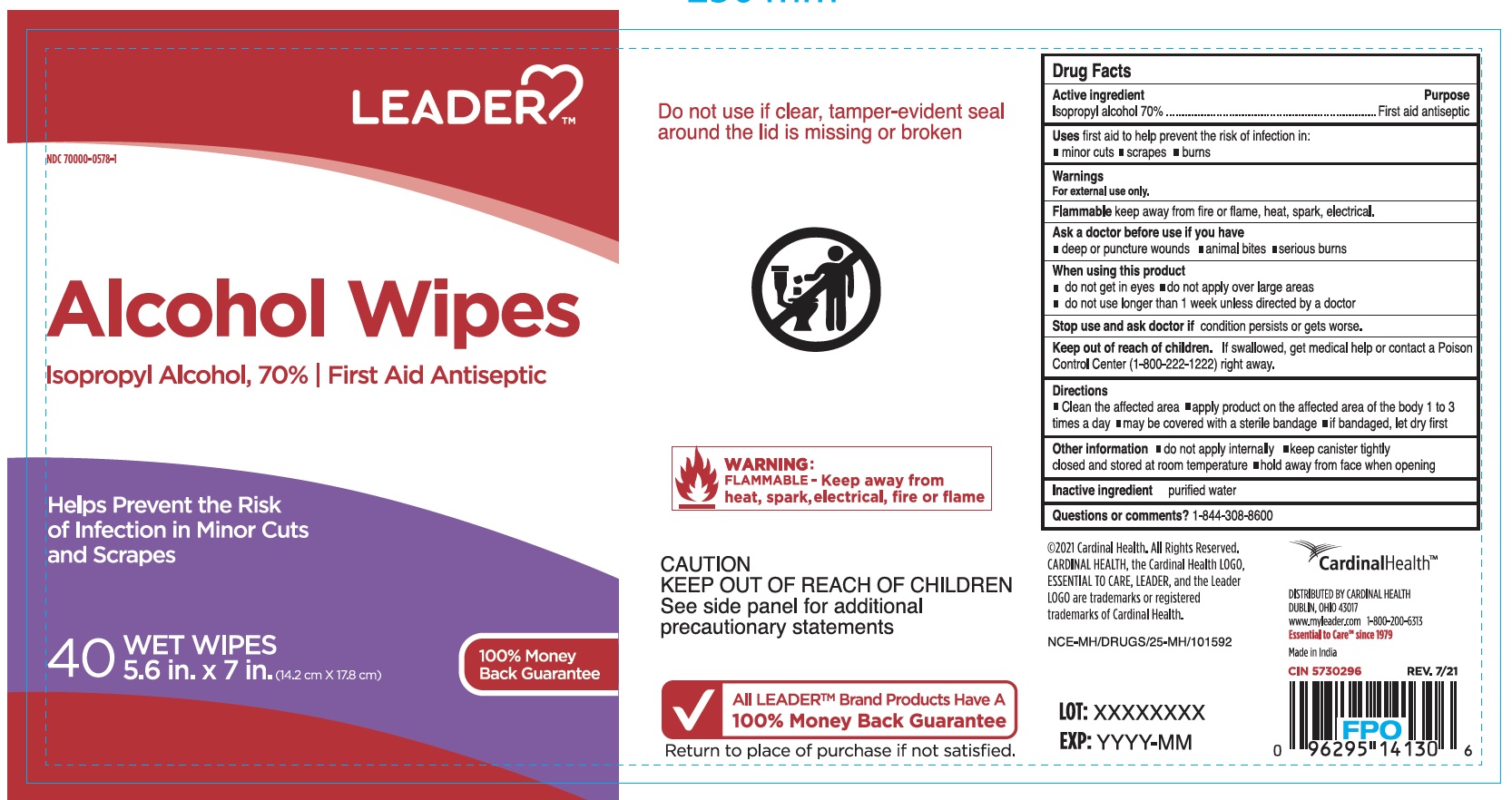 DRUG LABEL: Alcohol Wipe
NDC: 70000-0578 | Form: SWAB
Manufacturer: Cardinal Health
Category: otc | Type: HUMAN OTC DRUG LABEL
Date: 20251023

ACTIVE INGREDIENTS: ISOPROPYL ALCOHOL 70 mL/100 mL
INACTIVE INGREDIENTS: WATER

Leader Alcohol Wipes

ACTIVE INGREDIENT

Isopropyl alcohol 70%

PURPOSE

First aid antiseptic

INDICATIONS AND USAGE

first aid to help prevent the risk of infection in: minor cuts, scrapes, burns

WARNINGS

For external use only

SAFE HANDLING WARNING

Flammable keep away from fire or flame, heat, spark, eletrical

ASK DOCTOR

deep or puncture wounds

animal bites

serious burns

WHEN USING

do not get in eyes

do not apply over large areas

do not use longer than 1 week unless directed by doctor

Stop use and ask doctor if condition persists or gets worse

KEEP OUT OF REACH OF CHILDREN

If swallowed, get medical help or contact a Poison Control Center (1-800-222-1222) right away

DOSAGE AND ADMINISTRATION

Clean the affected area

apply product on the affected area of the body 1 to 3 times a day

may be covered with a sterile bandage

if bandaged, let dry first

OTHER SAFETY INFORMATION

do not apply internally

keep canister tightly closed and stored at room temperature

hold away from face when opening

INACTIVE INGREDIENT

purified water

Questions or comments? 1-844-308-8600